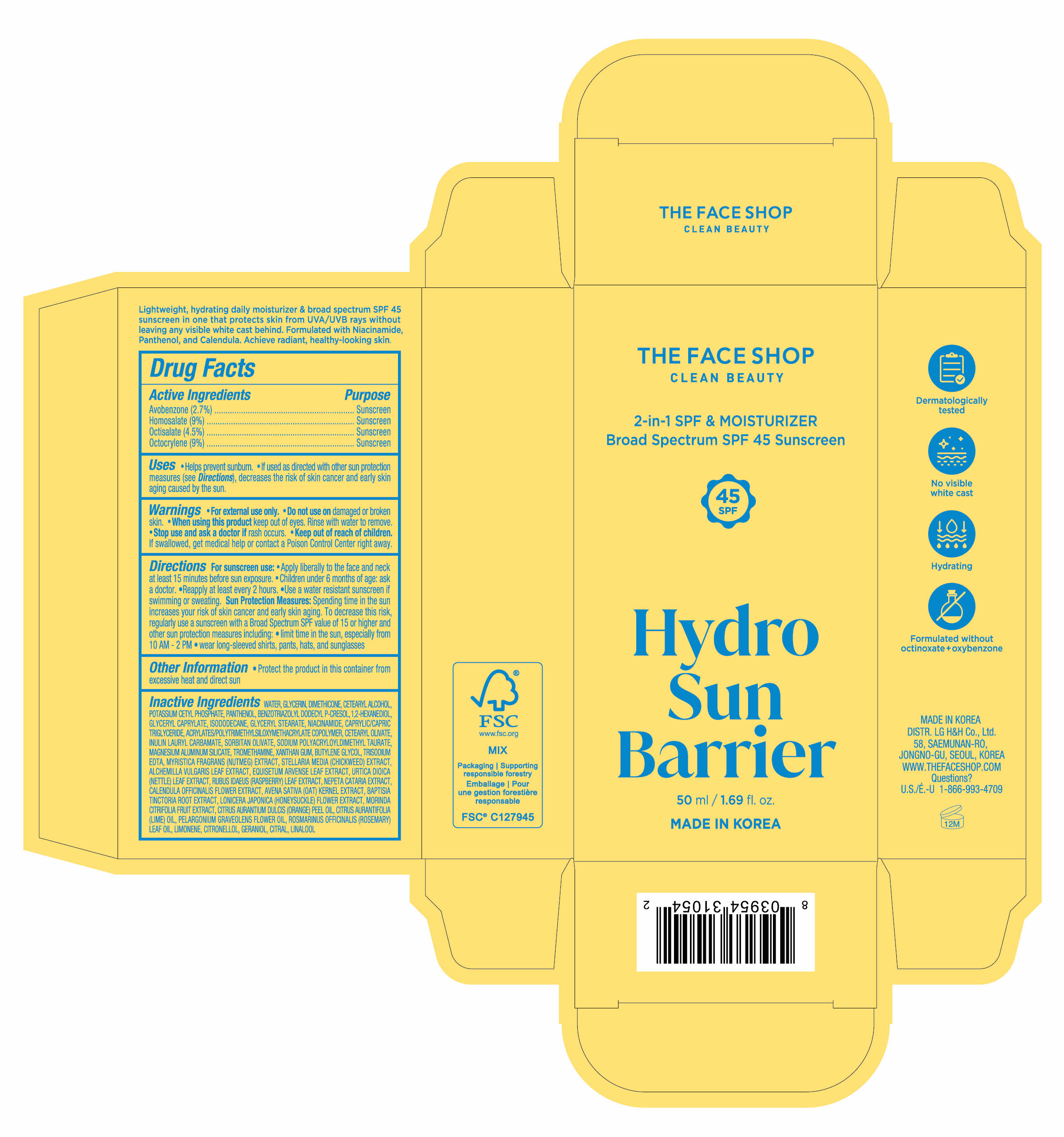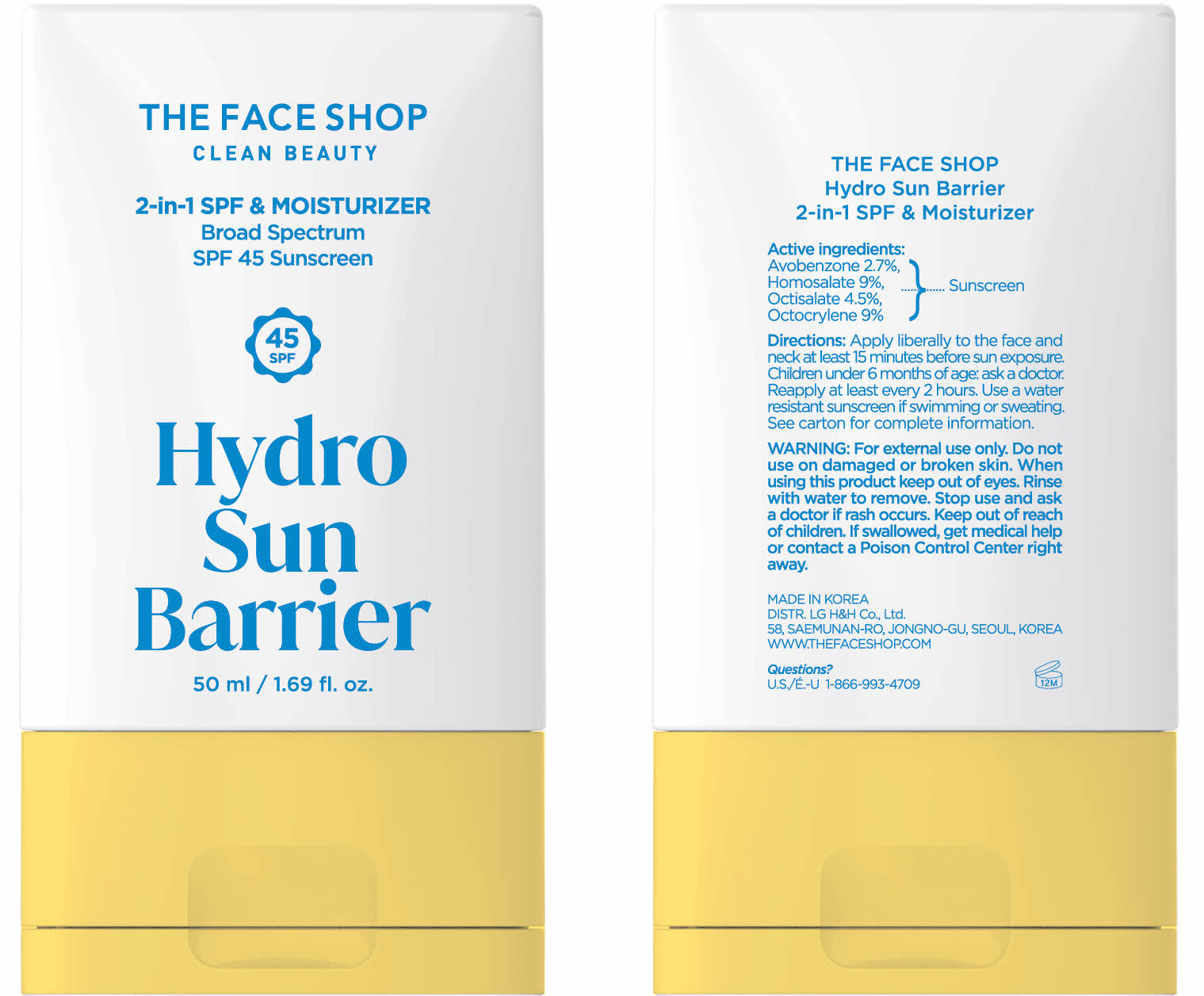 DRUG LABEL: The Face Shop Hydro Sun Barrier 2-in-1 SPF and Moisturizer
NDC: 53208-152 | Form: CREAM
Manufacturer: LG HOUSEHOLD & HEALTH CARE LTD.
Category: otc | Type: HUMAN OTC DRUG LABEL
Date: 20250408

ACTIVE INGREDIENTS: OCTISALATE 45 mg/1 mL; AVOBENZONE 27 mg/1 mL; HOMOSALATE 90 mg/1 mL; OCTOCRYLENE 90 mg/1 mL
INACTIVE INGREDIENTS: POTASSIUM CETYL PHOSPHATE; PANTHENOL; BENZOTRIAZOLYL DODECYL P-CRESOL; GLYCERYL CAPRYLATE; NIACINAMIDE; SODIUM POLYACRYLOYLDIMETHYL TAURATE; MAGNESIUM ALUMINUM SILICATE; NUTMEG; EQUISETUM ARVENSE LEAF POWDER; TROMETHAMINE; CETEARYL OLIVATE; XANTHAN GUM; SORBITAN OLIVATE; LONICERA JAPONICA FLOWER; PELARGONIUM GRAVEOLENS FLOWER OIL; RUBUS IDAEUS (RASPBERRY) LEAF POWDER; CALENDULA OFFICINALIS FLOWER; INULIN LAURYL CARBAMATE; ISODODECANE; BAPTISIA TINCTORIA ROOT; ROSMARINUS OFFICINALIS (ROSEMARY) LEAF OIL; ALCHEMILLA VULGARIS LEAF; NEPETA CATARIA; CITRUS AURANTIUM DULCIS (ORANGE) PEEL OIL; 1,2-HEXANEDIOL; GLYCERYL STEARATE; WATER; DIMETHICONE; CETEARYL ALCOHOL; CAPRYLIC/CAPRIC TRIGLYCERIDE; BUTYLENE GLYCOL; URTICA DIOICA LEAF; GLYCERIN; TRISODIUM EDTA; CITRAL; CITRONELLOL; LINALOOL, (+/-)-; CITRUS AURANTIFOLIA (LIME) OIL; LIMONENE, (+)-; MORINDA CITRIFOLIA FRUIT; OAT; GERANIOL

Active Ingredients

Avobenzone 2.7%

Homosalate 9%

Octisalate 4.5%

Octocrylene 9%

Purpose

Sunscreen

Uses

- Helps prevent sunburn.
- If used as directed with other sun protection measures (see Directions), decreases the risk of skin cancer and early skin aging caused by the sun.

WARNINGS

For external use only.

Do not use on damaged or broken skin.

When using

When using this product keep out of eyes. Rinse with water to remove.

Stop use

Stop use and ask a doctor if rash occurs.

Keep out of reach of children

DOSAGE AND ADMINISTRATION

If swallowed, get medical help or contact a Poison Control Center right away.

Directions

For sunscreen use:

- Apply liberally to the face and neck at least 15 minutes before sun exposure.
- Children under 6 months of age: ask a doctor.
- Reapply at least every 2 hours.
- Use a water resistant sunscreen if swimming or sweating.

Sun Protection Measures: Spending time in the sun increases your risk of skin cancer and early skin aging. To decrease this risk, regularly use a sunscreen with a Broad Spectrum SPF value of 15 or higher and other sun protection measures including:

- limit time in the sun, especially from 10AM-2PM
- wear long-sleeved shirts, pants, hats, and sunglasses

Other Information

- Protect the product in this container from excessive heat and direct sun

Inactive Ingredients

WATER, GLYCERIN, DIMETHICONE, CETEARYL ALCOHOL, POTASSIUM CETYL PHOSPHATE, PANTHENOL, BENZOTRIAZOLYL DODECYL P-CRESOL, 1,2-HEXANEDIOL, GLYCERYL CAPRYLATE, ISODODECANE, GLYCERYL STEARATE, NIACINAMIDE, CAPRYLIC/CAPRIC TRIGLYCERIDE, ACRYLATES/POLYTRIMETHYLSILOXYMETHACRYLATE COPOLYMER, CETEARYL OLIVATE, INULIN LAURYL CARBAMATE, SORBITAN OLIVATE, SODIUM POLYACRYLOYLDIMETHYL TAURATE, MAGNESIUM ALUMINUM SILICATE, TROMETHAMINE, XANTHAN GUM, BUTYLENE GLYCOL, TRISODIUM EDTA, MYRISTICA FRAGRANS (NUTMEG) EXTRACT, STELLARIA MEDIA (CHICKWEED) EXTRACT, ALCHEMILLA VULGARIS LEAF EXTRACT, EQUISETUM ARVENSE LEAF EXTRACT, URTICA DIOICA (NETTLE) LEAF EXTRACT, RUBUS IDAEUS (RASPBERRY) LEAF EXTRACT, NEPETA CATARIA EXTRACT, CALENDULA OFFICINALIS FLOWER EXTRACT, AVENA SATIVA (OAT) KERNEL EXTRACT, BAPTISIA TINCTORIA ROOT EXTRACT, LONICERA JAPONICA (HONEYSUCKLE) FLOWER EXTRACT, MORINDA CITRIFOLIA FRUIT EXTRACT, CITRUS AURANTIUM DULCIS (ORANGE) PEEL OIL, CITRUS AURANTIFOLIA (LIME) OIL, PELARGONIUM GRAVEOLENS FLOWER OIL, ROSMARINUS OFFICINALIS (ROSEMARY) LEAF OIL, LIMONENE, CITRONELLOL, GERANIOL, CITRAL, LINALOOL